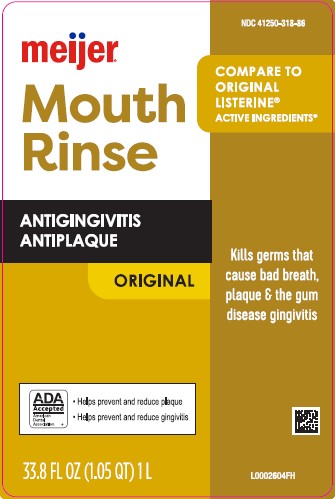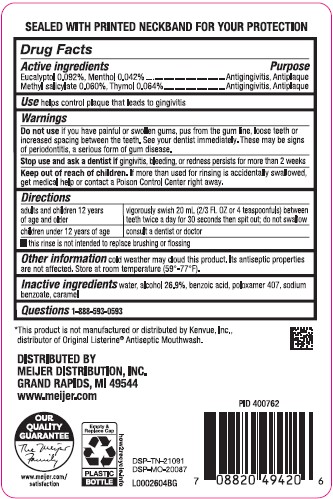 DRUG LABEL: Antiseptic Mouth Rinse
NDC: 41250-318 | Form: MOUTHWASH
Manufacturer: Meijer, Inc.
Category: otc | Type: HUMAN OTC DRUG LABEL
Date: 20260219

ACTIVE INGREDIENTS: EUCALYPTOL 0.92 mg/1 mL; MENTHOL 0.42 mg/1 mL; METHYL SALICYLATE 0.6 mg/1 mL; THYMOL 0.64 mg/1 mL
INACTIVE INGREDIENTS: WATER; ALCOHOL; BENZOIC ACID; POLOXAMER 407; CARAMEL; SODIUM BENZOATE

Meijer 318.003/318AH-AI
Antiseptic Mouthrinse

Tamper Evident Statement

Sealed With Printed Neckband For Your Protection

Active ingredients

Eucalyptol 0.092%

Menthol 0.042%

Methyl salicylate 0.060%

Thymol 0.064%

Use

Antigingivitis, Antiplaque

Use

helps control plaque that leads to gingivitis

Warnings

for this product

Do not use

if you have painful or swollen gums, pus from the gum line, loose teeth or increased spacing between the teeth. See your dentist immediately. These may be signs of periodontitis, a serious form of gum disease.

Stop use and ask a dentist if

gingivitis, bleeding, or redness persists for more than 2 weeks

Keep out of reach of children.

If more than used for rinsing is accidentally swallowed, get medical help or contact a Poison Control Center right away.

Directions

adults and children 12 years of age and older - vigorously swish 20 mL (2/3 FL OZ or 4 teaspoonfuls) between teeth twice a day for 30 seconds then spit out; do not swallow
children under 12 years of age - consult a dentist or doctor

- this rinse is not intended to replace brushing or flossing

Other information

cold weather may cloud this product. Its antiseptic properties are not affected. Store at room temperature (59°-77°F).

Inactive ingredients

water, alcohol 26.9%, benzoic acid, poloxamer 407, sodium benzoate, caramel

Questions

1-888-593-0593

Disclaimer

*This product is not manufactured or distributed by Kenvue, Inc, distributor of Original Listerine®Antiseptic Mouthwash.

Adverse Reactions

DISTRIBUTED BY

MEIJER DISTRIBUTION, INC.

GRAND RAPIDS, MI 49544

www. meijer.com

OUR QUALITY GUARANTEE

The Meijer Family

www.meijer.com/satisfaction

Empty & Replace Cap

PLASTIC BOTTLE

how2recycle.info

DSP-TN-21091

DSP-MO-20087

Principal display panel

NDC 41250-318-86

Compare to Original Listerine®Active Ingredients*

meijer®

Mouth Rinse

Antigngivitis

Antiplaque

ORIGINAL

Kills germs that cause bad breath, plaque and gingivitis

ADA Accepted

American Dental Association

- Helps prevent and reduce plaque
- Helps prevent and reduce gingivitis

33.8 FL OZ (1.05 QT) 1L